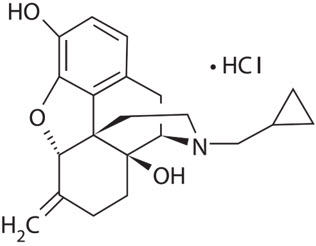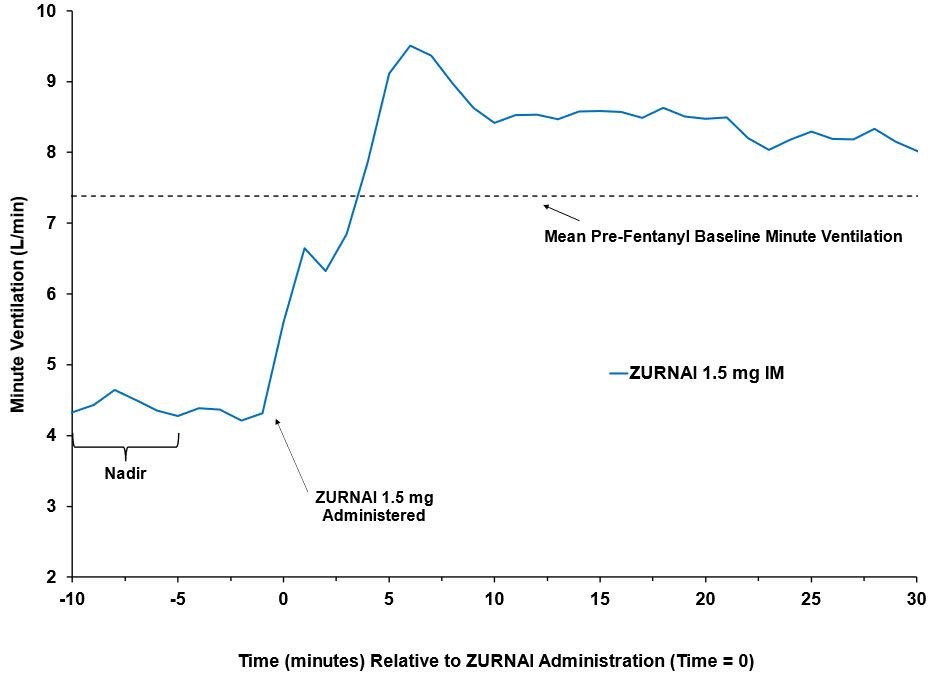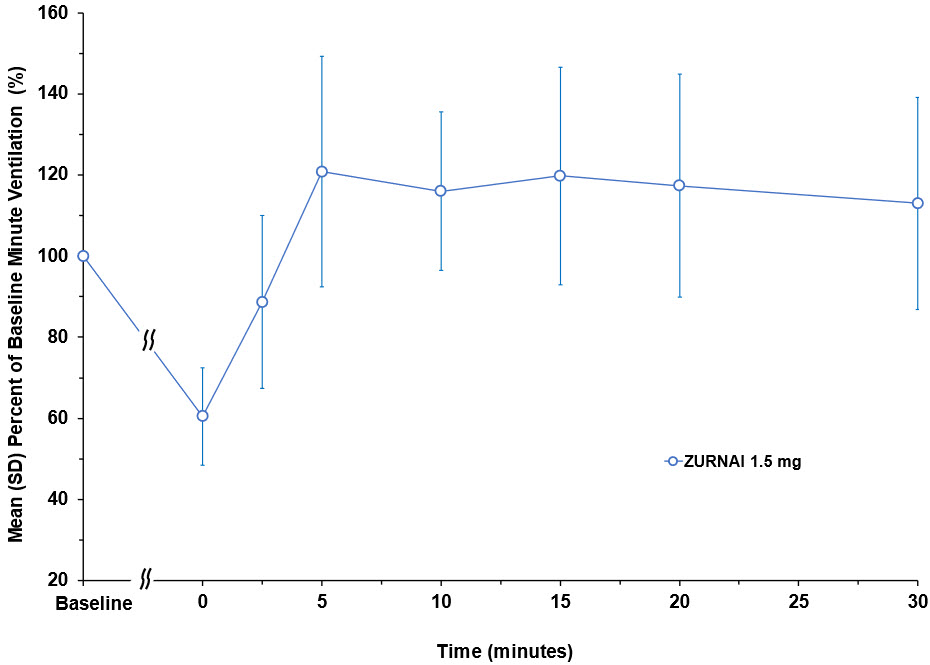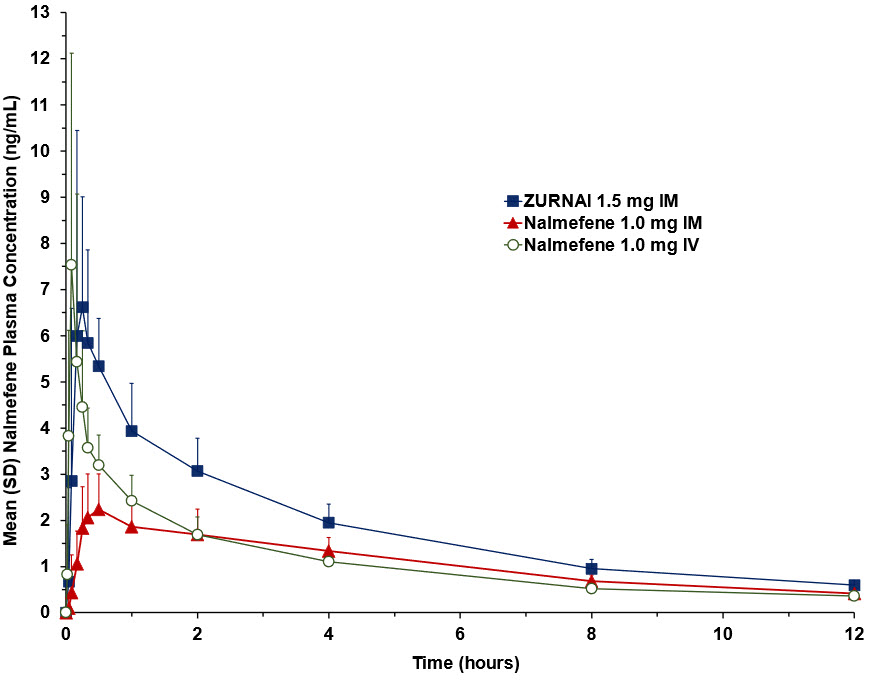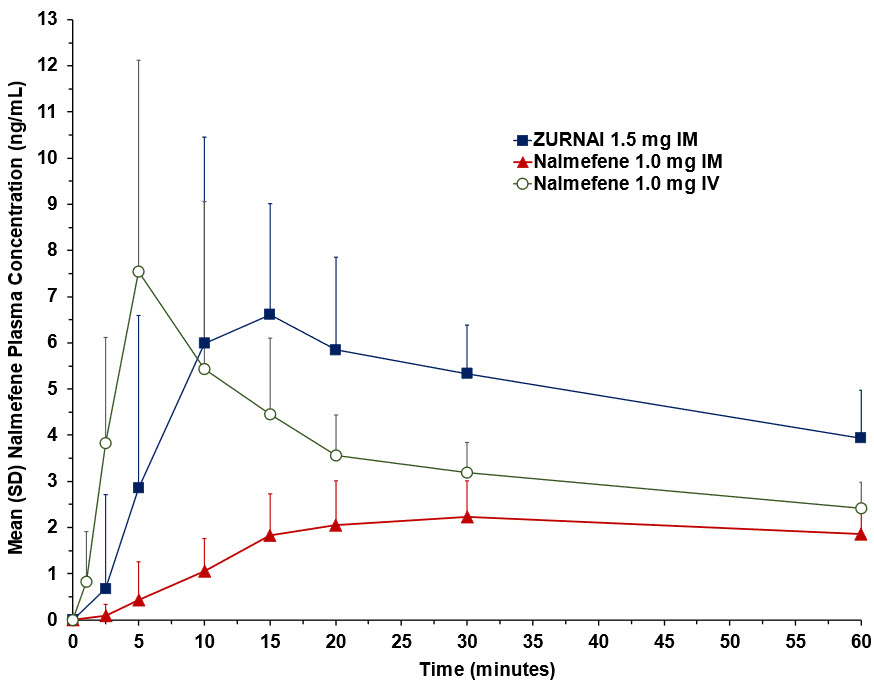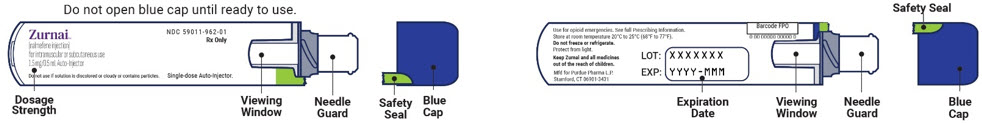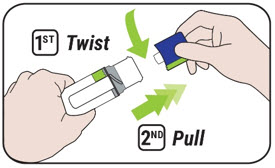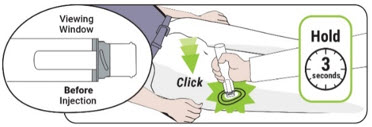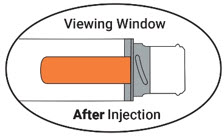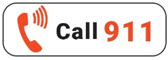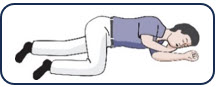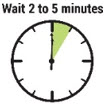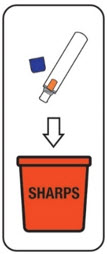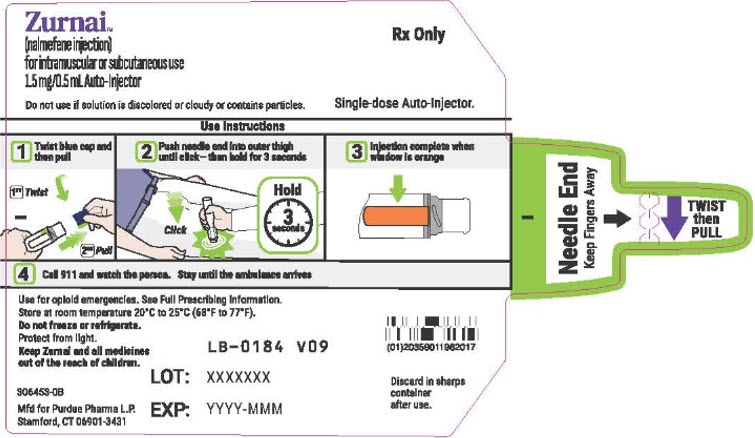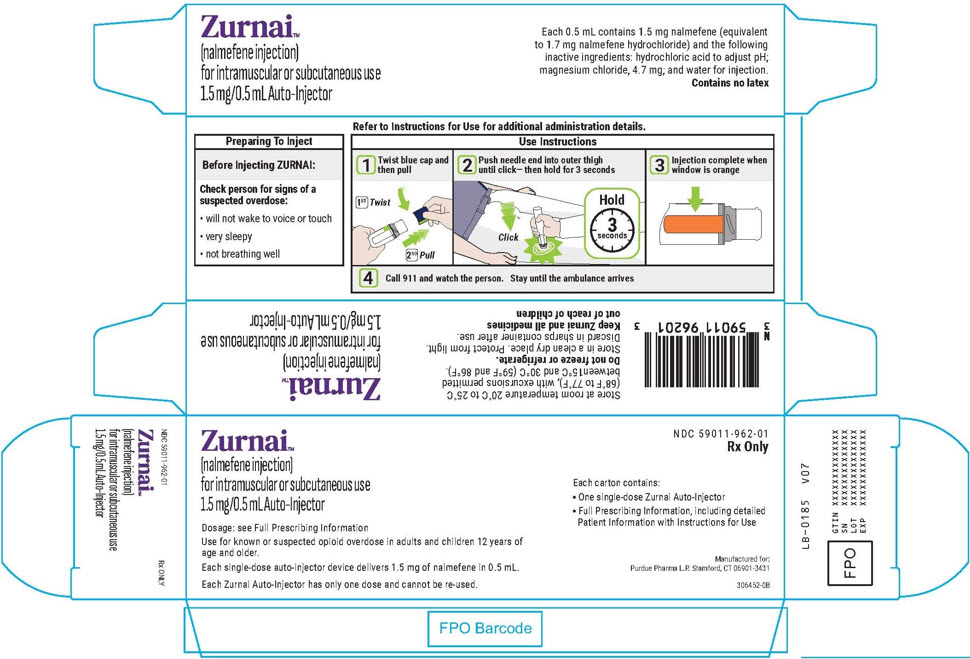 DRUG LABEL: Zurnai
NDC: 59011-962 | Form: INJECTION, SOLUTION
Manufacturer: Purdue Pharma L.P.
Category: prescription | Type: HUMAN PRESCRIPTION DRUG LABEL
Date: 20260224

ACTIVE INGREDIENTS: NALMEFENE HYDROCHLORIDE 1.5 mg/0.50 mL
INACTIVE INGREDIENTS: HYDROCHLORIC ACID; MAGNESIUM CHLORIDE; WATER

HIGHLIGHTS OF PRESCRIBING INFORMATION

These highlights do not include all the information needed to use ZURNAI™ safely and effectively. See full prescribing information for ZURNAI.
ZURNAI (nalmefene injection), for intramuscular or subcutaneous use
Initial U.S. Approval: 1995

1 INDICATIONS AND USAGE

ZURNAI is an opioid antagonist indicated for the emergency treatment of known or suspected opioid overdose induced by natural or synthetic opioids in adults and pediatric patients aged 12 years and older, as manifested by respiratory and/or central nervous system depression. (1)

ZURNAI is intended for immediate administration as emergency therapy in settings where opioids may be present. (1)

ZURNAI is not a substitute for emergency medical care. (1)

2 DOSAGE AND ADMINISTRATION

- ZURNAI is for intramuscular and subcutaneous use only. (2.1)
- Seek emergency medical care immediately after use. (2.1)
- Administer ZURNAI to the outer thigh, through clothing if necessary. (2.1)
- Administer additional doses of ZURNAI using a new ZURNAI auto-injector for each dose. If the patient does not respond or responds and then relapses into respiratory depression, additional doses of ZURNAI may be given every 2 to 5 minutes until emergency medical assistance arrives. (2.2)
- See Full Prescribing Information and Instructions for Use for important information on how to safely administer ZURNAI. (2.1)
- Additional supportive and/or resuscitative measures may be helpful while awaiting emergency medical assistance. (2.2)

3 DOSAGE FORMS AND STRENGTHS

Injection: 1.5 mg nalmefene base/0.5 mL in a prefilled, single-dose auto-injector (3)

4 CONTRAINDICATIONS

- Hypersensitivity to nalmefene hydrochloride or to any other ingredients in ZURNAI. (4)

5 WARNINGS AND PRECAUTIONS

- Risk of Recurrent Respiratory and CNS Depression: A recurrence of respiratory depression is possible, therefore, keep the patient under continued surveillance and administer repeat doses of ZURNAI using a new auto-injector with each dose while awaiting emergency medical assistance. (5.1)
- Risk of Limited Efficacy with Partial Agonists or Mixed Agonists/Antagonists: Reversal of respiratory depression by partial agonists or mixed agonist/antagonists such as buprenorphine and pentazocine, may be incomplete. Repeat doses may be required. (5.2)
- Precipitation of Severe Opioid Withdrawal: The use of ZURNAI in patients who are opioid dependent may precipitate opioid withdrawal. In neonates, opioid withdrawal may be life-threatening if not recognized and properly treated. Monitor for the development of opioid withdrawal. (5.3)
- Risk of Cardiovascular (CV) Effects: Abrupt postoperative reversal of opioid depression may result in adverse CV effects. These events have primarily occurred in patients who had preexisting CV disorders or received other drugs that may have similar adverse CV effects. Monitor these patients closely in an appropriate healthcare setting after use of nalmefene hydrochloride. (5.3)
- Risk of Opioid Overdose from Attempts to Overcome the Blockade: Attempts to overcome opioid withdrawal symptoms caused by opioid antagonists with high or repeated doses of exogenous opioids may lead to opioid intoxication and death. (5.4)

6 ADVERSE REACTIONS

Most common adverse reactions (incidence > 5%) are feeling hot, nausea, headache, dizziness, chills, vomiting, allodynia, palpitations, tinnitus, ear discomfort, feeling abnormal, burning sensation, hot flush, and irritability. (6)

To report Suspected Adverse Reactions, contact Purdue Pharma L.P. at 1-888-726-7535 or FDA at 1-800-FDA-1088 or www.fda.gov/medwatch.

FULL PRESCRIBING INFORMATION

1 INDICATIONS AND USAGE

ZURNAI is indicated for the emergency treatment of known or suspected opioid overdose induced by natural or synthetic opioids in adults and pediatric patients aged 12 years and older, as manifested by respiratory and/or central nervous system depression.

ZURNAI is intended for immediate administration as emergency therapy in settings where opioids may be present.

ZURNAI is not a substitute for emergency medical care.

2 DOSAGE AND ADMINISTRATION

2.1 Important Administration Instructions

- All approved nalmefene products achieve plasma concentrations that have been shown to be efficacious in reversing the effects of opioid overdose. Comparing different products on a nominal mg-for-mg basis may be misleading.
- ZURNAI is for intramuscular and subcutaneous use only.
- The device is ready to use. No device assembly is required.
- Do not prime or test prior to administration. ZURNAI delivers its entire contents automatically, upon injection.
- Inject ZURNAI into the anterolateral aspect of the thigh.
- ZURNAI can be administered through clothing if necessary.
- Do not reuse ZURNAI. Each ZURNAI device contains a single dose of nalmefene and cannot be reused.
- Because treatment of suspected opioid overdose must be performed by someone other than the patient, instruct the prescription recipient to inform those around them about the presence of ZURNAI and the Instructions for Use.
- Instruct the patient or caregiver to read the Instructions for Use at the time they receive a prescription for ZURNAI. Emphasize the following instructions to the patient or caregiver:
  - Administer ZURNAI as quickly as possible because prolonged respiratory depression may result in damage to the central nervous system or death.
  - Always seek emergency medical assistance after administration of the first dose of ZURNAI in the event of a suspected, potentially life-threatening opioid emergency. Keep the patient under continued surveillance until emergency personnel arrive.
  - Additional doses of ZURNAI may be required until emergency medical assistance becomes available.
  - If available, re-administer ZURNAI using a new auto-injector, every 2 to 5 minutes if the patient does not respond or responds and then relapses into respiratory depression.
  - Once the safety seal is broken and blue cap is removed, ZURNAI must be used immediately or disposed of properly. Do not attempt to replace the blue cap once it is removed.
  - Visually inspect ZURNAI through the viewing window for particulate matter and discoloration prior to administration. Do not administer unless the solution is clear, free of particulates, and the glass container is undamaged.
  - Administer ZURNAI according to the printed instructions on the device label, carton, and the Instructions for Use.
    ⮚ Place the needle guard of ZURNAI against the outer thigh. Press the needle end firmly into the injection site until you hear a click and then hold for 3 seconds. After 3 seconds, the viewing window should turn completely orange, signaling that ZURNAI has delivered the intended dose of nalmefene.
    ⮚ Remove ZURNAI from the outer thigh.
    ⮚ Call for emergency medical assistance immediately after administration of the first dose of ZURNAI.
    ⮚ Move the patient on their side (recovery position). Remain with the patient until emergency medical assistance arrives, even if the patient wakes up.

2.2 Dosing in Adults and Pediatric Patients 12 Years and Older

Initial Dosing:

The recommended dose of ZURNAI in adults and pediatric patients aged 12 years and older is 1.5 mg delivered by intramuscular or subcutaneous injection into the anterolateral aspect of the thigh, through clothing if necessary.

Repeat Dosing:

Seek emergency medical assistance as soon as possible after administration of the first dose of ZURNAI. The requirement for repeat doses of ZURNAI depends upon the amount, type, and route of administration of the opioid being antagonized.

If the patient responds to ZURNAI and subsequently relapses back into respiratory depression before emergency assistance arrives, administer an additional dose of ZURNAI using a new auto-injector and continue surveillance of the patient.

If the desired response is not obtained after 2 to 5 minutes, administer an additional dose of ZURNAI using a new auto-injector. If there is still no response and additional doses are available, administer additional doses of ZURNAI every 2 to 5 minutes using a new ZURNAI auto-injector for each dose until emergency medical assistance arrives.

Additional supportive and/or resuscitative measures may be helpful while awaiting emergency medical assistance.

2.3 Dosing Modifications Due to Partial Agonists or Mixed Agonists/Antagonists

Reversal of respiratory depression by partial agonists or mixed agonist/antagonists, such as buprenorphine and pentazocine, may be incomplete and require repeated administration of ZURNAI using a new auto-injector [see Warnings and Precautions (5.2)].

3 DOSAGE FORMS AND STRENGTHS

Injection: 1.5 mg/0.5 mL nalmefene (base), clear, colorless to light yellow solution in a pre-filled, single-dose auto-injector. Each ZURNAI auto-injector delivers 1.5 mg nalmefene (base) injection (0.5 mL).

4 CONTRAINDICATIONS

ZURNAI is contraindicated in patients known to be hypersensitive to nalmefene hydrochloride or to any other ingredients in the product.

5 WARNINGS AND PRECAUTIONS

5.1 Risk of Recurrent Respiratory and Central Nervous System Depression

Respiratory depression in the community overdose setting may be complex and involve the effects of multiple or unknown drugs, some of which may be long-acting opioids. While the duration of action of nalmefene is as long as most opioids, a recurrence of respiratory depression is possible, even after an apparently adequate initial response to ZURNAI treatment [see Clinical Pharmacology (12.3)]. Therefore, it is necessary to seek emergency medical assistance immediately after administration of the first dose of ZURNAI and to keep the patient under continued surveillance. A second dose may be necessary if there is recurrence of symptoms of opioid overdose. Additional supportive and/or resuscitative measures may be helpful while awaiting emergency medical assistance [see Dosage and Administration (2.2)].

5.2 Risk of Limited Efficacy with Partial Agonists or Mixed Agonist/Antagonists

Reversal of respiratory depression by partial agonists or mixed agonist/antagonists such as buprenorphine and pentazocine, may be incomplete. Repeat doses of ZURNAI may be required to antagonize buprenorphine because the latter has a long duration of action due to its slow rate of binding and subsequent slow dissociation from the opioid receptor [see Dosage and Administration (2.3)]. Buprenorphine antagonism is characterized by a gradual onset of the reversal effects and a decreased duration of action of the normally prolonged respiratory depression.

5.3 Precipitation of Severe Opioid Withdrawal

The use of ZURNAI in patients who are opioid dependent may precipitate opioid withdrawal characterized by the following signs and symptoms: body aches, diarrhea, tachycardia, fever, runny nose, sneezing, piloerection, sweating, yawning, nausea or vomiting, nervousness, restlessness or irritability, shivering or trembling, abdominal cramps, weakness, and increased blood pressure.

Abrupt postoperative reversal of opioid depression after using ZURNAI may result in nausea, vomiting, sweating, tremulousness, tachycardia, hypotension, hypertension, seizures, ventricular tachycardia and fibrillation, pulmonary edema, and cardiac arrest. Death, coma, and encephalopathy have been reported as sequelae of these events. These events have primarily occurred in patients who had pre-existing cardiovascular disorders or received other drugs that may have similar adverse cardiovascular effects. After use of ZURNAI, monitor patients with pre-existing cardiac disease or patients who have received medications with potential adverse cardiovascular effects for hypotension, ventricular tachycardia or fibrillation, and pulmonary edema in an appropriate healthcare setting. It has been suggested that the pathogenesis of pulmonary edema associated with the use of nalmefene is similar to neurogenic pulmonary edema, i.e., a centrally mediated massive catecholamine response leading to a dramatic shift of blood volume into the pulmonary vascular bed resulting in increased hydrostatic pressures.

ZURNAI is not indicated for use in patients less than 12 years of age. In neonates, opioid withdrawal may be life-threatening if not recognized and properly treated and may include the following signs and symptoms: convulsions, excessive crying, and hyperactive reflexes. Monitor the patient for the development of the signs and symptoms of opioid withdrawal. There may be clinical settings, particularly the postpartum period in neonates with known or suspected exposure to maternal opioid use, where it is preferable to avoid the abrupt precipitation of opioid withdrawal symptoms. In these settings, use an alternative, opioid antagonist product that can be titrated to effect and, where applicable, dosed according to weight [see Use in Specific Populations (8.4)].

5.4 Risk of Opioid Overdose from Attempts to Overcome the Blockade

ZURNAI is unlikely to produce acute withdrawal symptoms in non-opioid dependent patients. The use of ZURNAI in patients who are opioid dependent may precipitate opioid withdrawal. Attempting to overcome opioid withdrawal symptoms caused by opioid antagonists with high or repeated doses of exogenous opioids could lead to opioid intoxication and death.

Inform patients of the potential consequences of trying to overcome the opioid blockade. Get emergency medical assistance as soon as possible after use of ZURNAI regardless of withdrawal symptoms.

6 ADVERSE REACTIONS

The following serious adverse reactions are described elsewhere in the labeling:

- Recurrent Respiratory and Central Nervous System Depression [see Warnings and Precautions (5.1)]
- Precipitation of Severe Opioid Withdrawal [see Warnings and Precautions (5.3)]

6.1 Clinical Trial Experience

Adult Clinical Trial Experience

Because clinical trials are conducted under widely varying conditions, adverse reaction rates observed in the clinical trials of a drug cannot be directly compared to rates in the clinical trials of another drug and may not reflect the rates observed in practice.

The safety of ZURNAI is supported by pharmacokinetic and pharmacodynamic studies of ZURNAI in healthy subjects in a normal state and under steady state opioid agonism. The following adverse reactions were observed.

In a pharmacokinetic study (NAL1005) of 21 healthy adult volunteers exposed to one dose of ZURNAI the most common adverse reactions were: dizziness and headache.

In a pharmacodynamic study (NAL1004) of 23 healthy adult volunteers exposed to one dose of ZURNAI, the most common adverse reactions were: feeling hot, chills, nausea, allodynia, and headache.

Table 1: Relative Frequencies of Most Common Adverse Reactions that Occurred in Greater than 5% of Subjects in Study NAL1004 and Study NAL1005 (pooled dataset)
 | Nalmefene Auto-Injector 1.5 mg IM
System Organ Class Preferred Term | Pooled NAL1004 and NAL1005 N=44 n (%) | Study NAL1004 N=23 n (%) | Study NAL1005 N=21 n (%)
Any AR | 28 (63.6) | 21 (91.3) | 7 (33.3)
Cardiac disorders
Palpitations | 4 (9.1) | 4 (17.4) | 0
Ear and labyrinth disorders
Tinnitus | 4 (9.1) | 4 (17.4) | 0
Ear discomfort | 3 (6.8) | 3 (13.0) | 0
Gastrointestinal disorders
Nausea | 8 (18.2) | 6 (26.1) | 2 (9.5)
Vomiting | 5 (11.4) | 3 (13.0) | 2 (9.5)
General disorders and administration site conditions
Feeling hot | 11 (25.0) | 11 (47.8) | 0
Chills | 6 (13.6) | 6 (26.1) | 0
Feeling abnormal | 3 (6.8) | 3 (13.0) | 0
Nervous system disorders
Dizziness | 7 (15.9) | 4 (17.4) | 3 (14.3)
Headache | 8 (18.2) | 5 (21.7) | 3 (14.3)
Allodynia | 5 (11.4) | 5 (21.7) | 0
Burning sensation | 3 (6.8) | 3 (13.0) | 0
Psychiatric disorders
Irritability | 3 (6.8) | 3 (13.0) | 0
Vascular disorders
Hot flush | 3 (6.8) | 3 (13.0) | 0

Adverse reaction information was obtained following administration of nalmefene hydrochloride injection to 152 healthy volunteers and to 1127 patients in controlled clinical trials for the treatment of opioid overdose or for postoperative opioid reversal.

TABLE 2: Relative Frequencies of Common Adverse Reactions with an Incidence Greater than 1% (all patients, all clinical settings)
Adverse Reaction | Nalmefene N=1127 | Placebo N=77
Nausea | 18% | 6%
Vomiting | 9% | 4%
Tachycardia | 5% | -
Hypertension | 5% | -
Postoperative pain | 4% | N/A
Fever | 3% | -
Dizziness | 3% | 1%
Headache | 1% | 4%
Chills | 1% | -
Hypotension | 1% | -
Vasodilatation | 1% | -

Incidence less than 1%

CARDIOVASCULAR: Bradycardia, arrhythmia

DIGESTIVE: Diarrhea, dry mouth

NERVOUS SYSTEM: Somnolence, depression, agitation, nervousness, tremor, confusion, withdrawal syndrome, myoclonus

RESPIRATORY: Pharyngitis

SKIN: Pruritus

UROGENITAL: Urinary retention

The incidence of adverse events was highest in patients who received more than the recommended dose of nalmefene hydrochloride injection.

6.2 Postmarketing Experience

The following adverse reactions have been identified during post-approval use of nalmefene. Because these reactions are reported voluntarily from a population of uncertain size, it is not always possible to reliably estimate their frequency or establish a causal relationship to drug exposure.

Abrupt reversal of opioid depression using nalmefene in both postoperative and emergency department settings has resulted in nausea, vomiting, sweating, tremulousness, seizures, and cardiovascular instability including tachycardia, hypotension, hypertension, ventricular tachycardia and fibrillation, pulmonary edema, and cardiac arrest. Death, coma, and encephalopathy have been reported as sequelae of these events. These events have primarily occurred in patients who had pre-existing cardiovascular disorders or received other drugs that may have similar adverse cardiovascular effects.

In persons who were physically dependent on opioids, abrupt reversal of opioid effects has precipitated an acute withdrawal syndrome. Signs and symptoms have included: body aches, fever, sweating, runny nose, sneezing, piloerection, yawning, weakness, shiver or trembling, nervousness, restlessness or irritability, diarrhea, nausea or vomiting, abdominal cramps, increased blood pressure, and tachycardia. In some patients, there may be aggressive behavior upon abrupt reversal of an opioid overdose. In the neonate, opioid withdrawal symptoms also included convulsions, excessive crying, and hyperactive reflexes.

8 USE IN SPECIFIC POPULATIONS

8.1 Pregnancy

Risk Summary

Life-sustaining therapy for opioid overdose should not be withheld [see Clinical Considerations]. There are no available data on nalmefene use in pregnant women to evaluate for a drug-associated risk of major birth defects or miscarriage. In animal reproduction studies, no effects on embryo-fetal development were observed in rats and rabbits treated with nalmefene [see Data].

The background risk of major birth defects and miscarriage for the indicated population is unknown. All pregnancies have a background risk of birth defect, loss, or other adverse outcomes. In the U.S. general population, the estimated background risk of major birth defects and miscarriage in clinically recognized pregnancies is 2% to 4% and 15% to 20%, respectively.

Clinical Considerations

Disease-associated maternal and/or embryo/fetal risk

An opioid overdose is a medical emergency and can be fatal for the pregnant woman and fetus if left untreated. Treatment with ZURNAI for opioid overdose should not be withheld because of potential concerns regarding the effects of ZURNAI on the fetus.

Data

Animal Data

Reproduction studies have been performed in rats and rabbits by oral administration and in rabbits by intravenous administration of nalmefene. No effects on embryo-fetal development were observed at rat oral doses up to 1200 mg/m^2/day and rabbit oral doses up to 2400 mg/m^2/day, and intravenous dose up to 96 mg/m^2/day, which is 52 times the human dose of 3.0 mg (two ZURNAI administrations) based on body surface area comparison. The treatment in rats did not affect offspring survival.

8.2 Lactation

Risk Summary

There are no data on the presence of nalmefene and its metabolites in human milk, the effects of nalmefene on the breastfed child, or the effects on milk production. Nalmefene and its metabolites are present in rat milk [see Data]. When a drug is present in animal milk, it is likely that the drug will be present in human milk.

Data

Nalmefene and its metabolites were secreted into rat milk, reaching concentrations approximately three times those in plasma at one hour and decreasing to about half the corresponding plasma concentrations by 24 hours following bolus administration. The concentration of nalmefene in animal milk does not necessarily predict the concentration of drug in human milk.

8.4 Pediatric Use

The safety and effectiveness of ZURNAI for the emergency treatment of known or suspected opioid overdose, as manifested by respiratory and/or central nervous system depression, have been established in pediatric patients aged 12 years and older.

Use for this indication in this age group is supported by adult studies and pharmacokinetic simulation [see Clinical Pharmacology (12.3)]. There have been no studies conducted to evaluate the use of ZURNAI in pediatric patients.

The safety and effectiveness of ZURNAI for the emergency treatment of known or suspected opioid overdose, as manifested by respiratory and/or central nervous system depression, have not been established in pediatric patients younger than 12 years of age.

8.5 Geriatric Use

Clinical studies of nalmefene hydrochloride injection did not include sufficient number of subjects aged 65 and over to determine whether they respond differently from younger subjects. Other reported clinical experience has not identified differences in responses between the elderly and younger patients. Geriatric patients have a greater frequency of decreased hepatic, renal, or cardiac function, or other drug therapy. Therefore, the systemic exposure of nalmefene can be higher in these patients.

8.6 Hepatic Impairment

Hepatic impairment substantially reduces the clearance of nalmefene [see Clinical Pharmacology (12.3)]. For single episodes of opioid antagonism, adjustment of ZURNAI dosage is not required.

8.7 Renal Impairment

Renal impairment substantially reduces the clearance of nalmefene [see Clinical Pharmacology (12.3)]. For single episodes of opioid antagonisms, adjustment of ZURNAI dosage is not required.

11 DESCRIPTION

ZURNAI™ (nalmefene injection) is a sterile, pre-filled, single-dose auto-injector designed to deliver a dose of 1.5 mg nalmefene (provided as nalmefene hydrochloride) in 0.5 mL.

Nalmefene hydrochloride, an opioid antagonist, is a 6-methylene analogue of naltrexone. The molecular structure of nalmefene is presented below:

Molecular Formula: C21H25NO3∙HCl

Molecular Weight: 375.9, CAS# 58895-64-0

Chemical Name: 17-(Cyclopropylmethyl)-4,5α-epoxy-6-methylenemorphinan-3,14-diol, hydrochloride salt

Nalmefene is a white to off-white crystalline powder which is freely soluble in water up to 130 mg/mL and slightly soluble in chloroform up to 0.13 mg/mL, with a pKa of 7.63.

Each ZURNAI auto-injector delivers 1.5 mg nalmefene (equivalent to 1.7 mg nalmefene hydrochloride) in 0.5 mL solution. The pH range is 3.5 to 4.5.

The inactive ingredients in ZURNAI nalmefene injection include: hydrochloric acid to adjust pH; magnesium chloride, 4.7 mg; and water for injection.

12 CLINICAL PHARMACOLOGY

12.1 Mechanism of Action

ZURNAI is an antagonist at opioid receptors.

12.2 Pharmacodynamics

Nalmefene reverses the effects of natural and synthetic opioids, including respiratory depression, sedation, and hypotension. Pharmacodynamic studies have shown that nalmefene injection has a longer duration of action than naloxone injection at fully reversing doses. Nalmefene has no opioid agonist activity.

The effect of ZURNAI was studied in an experimental clinical opioid-induced respiratory depression (OIRD) model in twenty-four opioid-experienced, non-opioid dependent subjects (NAL1004). This model assessed changes in minute ventilation (MV) during administration of a 3-step intravenous fentanyl infusion. In step 1, fentanyl was infused until MV nadir (functional OIRD) was achieved. MV nadir was defined as a 50% reduction in MV from baseline or the MV reduction achieved following the maximum permitted fentanyl titration. Following attainment of MV nadir, the fentanyl infusion rate was decreased (step 2) to maintain the fentanyl concentrations. ZURNAI was administered at 10 minutes following MV nadir. Ten minutes following ZURNAI administration, the fentanyl infusion rate was further decreased (step 3) to maintain constant fentanyl concentrations for the remaining duration of the reversal session.

Following ZURNAI administration the time to onset of effect, that is onset of reversal of respiratory depression, was observed between 2.5 to 5 minutes (Figure 1 and Figure 2). At 5 minutes mean change in MV from nadir was 4.42 L/min (Figure 1). Full recovery of respiratory drive was noted between 5 and 15 minutes after ZURNAI administration (Figure 1 and Figure 2).

Figure 1: Reversal of Fentanyl-Induced Respiratory Depression in adult healthy volunteers treated with ZURNAI (nalmefene)

Figure 2: Percent Recovery of Respiratory Drive after Fentanyl Infusion in Minute Ventilation (Mean SD) in Adult Healthy Volunteers with ZURNAI 1.5 mg

Nalmefene is not known to produce respiratory depression, psychotomimetic effects, or pupillary constriction. No pharmacological activity was observed when nalmefene was administered in the absence of opioid agonists.

Nalmefene has not been shown to produce tolerance, physical dependence, or abuse potential.

Nalmefene can produce acute withdrawal symptoms in individuals who are opioid dependent.

12.3 Pharmacokinetics

In a pharmacokinetic study (NAL1005) in 24 healthy adult subjects, the relative bioavailability of one dose of ZURNAI administered intramuscularly was compared to a single dose of nalmefene 1.0 mg administered as an intramuscular injection. The pharmacokinetic parameters obtained in this study are shown in Table 3 and the plasma concentration time profiles of nalmefene are presented in Figure 3.

Table 3: Geometric Mean (CV%) Nalmefene PK Parameters after Administration of 1.5 mg ZURNAI Intramuscular (IM), 1.0 mg Nalmefene IM, and 1.0 mg Nalmefene Intravenous (IV)
Parameter | ZURNAI 1.5 mg | Nalmefene IM 1.0 mg | Nalmefene IV 1.0 mg
Tmax (h) [Tmax presented as median (range)] | 0.25 (0.083-1.00) | 0.50 (0.083-2.00) | 0.083 (0.083 -0.25)
Cmax (ng/mL) | 7.37 (47.5) | 2.39 (32.6) | 6.94 (55.7)
AUC0-2.5min (ng-hr/mL) [Arithmetic mean] | 0.011 (288) | 0.001 (241) | 0.062 (56.1)
AUC0-5min (ng-hr/mL) | 0.077 (144) | 0.010 (209) | 0.299 (40.4)
AUC0-10min (ng-hr/mL) | 0.320 (85.8) | 0.047 (107) | 0.768 (46.2)
AUC0-15min (ng-hr/mL) | 0.831 (62.7) | 0.152 (64.8) | 1.16 (46.1)
AUC0-20min (ng-hr/mL) | 1.31 (51.3) | 0.315 (48.3) | 1.50 (41.7)
AUC0-30min (ng-hr/mL) | 2.24 (39.3) | 0.647 (40.7) | 2.07 (34.0)
AUC0-inf (ng-hr/mL) | 30.53 (16.0) | 17.98 (21.0) | 18.22 (15.3)
Frel (%) | 113 (13.0) | NA | NA
T½ (h) | 9.07 (26.6) | 7.74 (24.3) | 9.12 (16.5)
NA = Not applicable.

Figure 3: Mean Plasma Concentration-Time Profiles of Nalmefene (a) 0-12 hours and (b) 0- 60 minutes Following Administration of 1.5 mg ZURNAI Intramuscular (IM), 1.0 mg Nalmefene IM, and 1.0 mg Nalmefene Intravenous (IV)

(a)

(b)

Absorption

After administration of one ZURNAI to healthy adult subjects, the median Tmax for ZURNAI was 0.250 hours, compared to 0.5 hours for the intramuscular nalmefene 1 mg injection.

Based on dose-normalized area under the curve (AUCinf), the mean bioavailability of ZURNAI was 1.13 (Frel) relative to intramuscular administration of nalmefene 1 mg and was 1.15 (Fabs) relative to intravenous administration of nalmefene 1 mg.

Distribution

Following a 1 mg parenteral dose, nalmefene was rapidly distributed. In a study of brain receptor occupancy, a 1 mg dose of nalmefene blocked over 80% of brain opioid receptors within 5 minutes after administration. The apparent volumes of distribution centrally (Vc) and at steady state (Vdss) are 3.9 ± 1.1 L/kg and 8.6 ± 1.7 L/kg, respectively. Ultrafiltration studies of nalmefene have demonstrated that 45% (CV 4.1%) is bound to plasma proteins over a concentration range of 0.1 to 2 mcg/mL. An in vitro determination of the distribution of nalmefene in human blood demonstrated that nalmefene distributed 67% (CV 8.7%) into red blood cells and 39% (CV 6.4%) into plasma. The whole blood to plasma ratio was 1.3 (CV 6.6%) over the nominal concentration range in whole blood from 0.376 to 30 ng/mL.

Elimination

After administration of ZURNAI to healthy adult subjects, plasma concentrations have a terminal elimination half-life of 9.07 (%CV 26.2) hours. Following a 1 mg parenteral dose, the apparent clearance of nalmefene is 55.46 (%CV 8.41) L/hr.

Metabolism

Nalmefene is metabolized by the liver, primarily by glucuronide conjugation.

Nalmefene is also metabolized to trace amounts of an N-dealkylated metabolite. Nalmefene glucuronide is inactive and the N-dealkylated metabolite has minimal pharmacological activity.

Excretion

Nalmefene and its metabolites are excreted in the urine. Less than 5% of nalmefene is excreted in the urine unchanged. Seventeen percent (17%) of the nalmefene dose is excreted in the feces. The plasma concentration-time profile in some subjects suggests that nalmefene undergoes enterohepatic recycling.

Specific Populations

Geriatric Population

In previous studies with nalmefene hydrochloride injection, dose proportionality was observed in nalmefene AUC0-inf following 0.5 to 2 mg intravenous administration to elderly male subjects. Following a 1 mg intravenous nalmefene dose, there were no significant differences between young (19 to 32 years) and elderly (62 to 80 years) adult male subjects with respect to plasma clearance, steady-state volume of distribution, or half-life. There was an apparent age-related decrease in the central volume of distribution (young: 3.9 ± 1.1 L/kg, elderly: 2.8 ± 1.1 L/kg) that resulted in a greater initial nalmefene concentration in the elderly group. While initial nalmefene plasma concentrations were transiently higher in the elderly, it would not be anticipated that this population would require dosing adjustment. No clinical adverse events were noted in the elderly following the 1 mg intravenous nalmefene dose.

Pediatric Patients

No pharmacokinetic studies were conducted with ZURNAI in pediatric patients. Based on population PK simulations, compared to an adult population (mean weight 76 kg), 12-year-old subjects with a median weight 49 kg, range 33 to 71 kg are expected to have 27% higher mean Cmax and 15% higher mean AUC0-∞ [See Use in Specific Populations (8.4)].

Male and Female Patients

There is insufficient experience with the use of nalmefene hydrochloride injection to detect sex variations in pharmacokinetics.

Patients with Renal Impairment

The pharmacokinetics of ZURNAI have not been studied in renally impaired subjects. In previous studies with nalmefene hydrochloride injection, there was a statistically significant 27% decrease in plasma clearance of nalmefene in the end-stage renal disease (ESRD) population during interdialysis (0.57 ± 0.20 L/hr/kg) and a 25% decreased plasma clearance in the ESRD population during intradialysis (0.59 ± 0.18 L/hr/kg) compared to normal patients (0.79 ± 0.24 L/hr/kg). The elimination half-life was prolonged in ESRD patients from 10.2 ± 2.2 hours in normal patients to 26.1 ± 9.9 hours.

Patients with Hepatic Impairment

The pharmacokinetics of ZURNAI have not been studied in hepatically impaired subjects. In previous studies with nalmefene hydrochloride injection, in subjects with hepatic disease, when compared to matched normal controls, had a 28.3% decrease in plasma clearance of nalmefene (0.56 ± 0.21 L/hr/kg versus 0.78 ± 0.24 L/hr/kg, respectively). Elimination half-life increased from 10.2 ± 2.2 hours to 11.9 ± 2.0 hours in the hepatically impaired. No dosage adjustment is recommended since nalmefene will be administered as an acute course of therapy.

Low Body Weight Patients and High Body Weight Patients

The effect of weight on nalmefene PK following a single dose of 1.5 mg ZURNAI administration was assessed using population pharmacokinetic simulations. Compared to the mean PK values across the full population in the PK dataset (median weight 76 kg), the 1st quartile of body weight (54.0 to 67.3 kg) had + 17.6% higher Cmax and + 13.4% higher AUC0-∞ whereas the 4th quartile of body weight (86.8 to 117.1 kg) had – 15.3% lower Cmax and – 11.8% lower AUC0-∞.

13 NONCLINICAL TOXICOLOGY

13.1 Carcinogenesis, Mutagenesis, Impairment of Fertility

Carcinogenesis

Long-term animal studies to evaluate the carcinogenic potential of nalmefene have not been completed.

Mutagenesis

Nalmefene did not have mutagenic activity in the Ames test with five bacterial strains or the mouse lymphoma assay. Clastogenic activity was not observed in the mouse micronucleus test or in the cytogenic bone marrow assay in rats. However, nalmefene did exhibit a weak but significant clastogenic activity in the human lymphocyte metaphase assay in the absence but not in the presence of exogenous metabolic activation.

Impairment of Fertility

Oral administration of nalmefene up to 1200 mg/m^2/day did not affect fertility in rats.

16 HOW SUPPLIED/STORAGE AND HANDLING

16.1 How Supplied

Each single-dose auto-injector delivers 1.5 mg of nalmefene in 0.5 mL. Each carton contains one single-dose ZURNAI (nalmefene injection).

NDC 59011-962-01: One carton containing one single-dose auto-injector.

ZURNAI is not made with natural rubber latex.

16.2 Storage and Handling

Store at controlled room temperature 20°C to 25°C (68°F to 77°F), with excursions permitted between 15°C and 30°C (59°F and 86°F).

During storage, check ZURNAI through the viewing window of the auto-injector every 30 days. The liquid should be clear, colorless to light yellow. If the ZURNAI liquid is discolored, cloudy, or contains solid particles, replace it with a new ZURNAI.

DO NOT FREEZE OR REFRIGERATE. Store in a clean dry place. Protect from light.

Keep ZURNAI in the carton until use.

Store ZURNAI securely and dispose of properly in a sharps container. For detailed disposal instructions, see the Instructions for Use.

KEEP ZURNAI AND ALL MEDICINES OUT OF THE REACH OF CHILDREN.

Before using, check to make sure the solution in the auto-injector is not discolored. Replace ZURNAI if the solution is discolored or contains a precipitate.

Each ZURNAI can only be used one time and cannot be re-used.

17 PATIENT COUNSELING INFORMATION

Advise the patient and family members or caregivers to read the FDA-approved patient labeling (Patient Information and Instructions for Use).

Instruct patients and their family members or caregivers to become familiar with all information contained in the carton as soon as they receive ZURNAI.

Recognition of Opioid Overdose

Instruct patients and their family members or caregivers about how to recognize the signs and symptoms of an opioid overdose, such as the following:

- Extreme somnolence – inability to awaken a patient verbally or upon a firm sternal rub
- Respiratory depression – this can range from slow or shallow respiration to no respiration in a patient who is unarousable
- Other signs and symptoms that may accompany somnolence and respiratory depression include the following:
  - Miosis
  - Bradycardia and/or hypotension

Risk of Recurrent Respiratory and Central Nervous System Depression

While the duration of action of nalmefene is as long as most opioids, instruct patients and their family members or caregivers that they must seek immediate emergency medical assistance after administration of the first dose of ZURNAI, and keep the patient under continued surveillance even after an apparently adequate initial response to ZURNAI. A second dose may be necessary if there is recurrence of symptoms of opioid overdose [see Dosage and Administration (2.2), Warnings and Precautions (5.1)].

Limited Efficacy for/with Partial Agonists or Mixed Agonist/Antagonists

Instruct patients and their family members or caregivers that the reversal of respiratory depression caused by partial agonists or mixed agonist/antagonists, such as buprenorphine and pentazocine, may be incomplete and may require repeated administration of ZURNAI, using a new ZURNAI auto-injector each time [see Dosage and Administration (2.2), Warnings and Precautions (5.2)].

Precipitation of Severe Opioid Withdrawal

Instruct patients and their family members or caregivers that the use of ZURNAI in patients who are opioid dependent may precipitate opioid withdrawal [see Warnings and Precautions (5.3), Adverse Reactions (6)].

Administration Instructions

Instruct patients and their family member or caregivers to:

- Ensure ZURNAI is readily available in locations where persons may be intentionally or accidentally exposed to an opioid overdose (i.e., opioid emergencies).
- Use ZURNAI one time only. DO NOT test or prime prior to use [see Dosage and Administration (2.1)].
- Carefully read the Instructions for Use that comes with ZURNAI.
- Administer ZURNAI as quickly as possible if a person is unresponsive and an opioid overdose is suspected, even when in doubt, because prolonged respiratory depression may result in damage to the central nervous system or death. ZURNAI is not a substitute for emergency medical care [see Dosage and Administration (2.1)].
- Administer ZURNAI directly into the outer thigh. Press the needle end firmly into the injection site (through clothing, if necessary) and hold for 3 seconds [see Dosage and Administration (2.1)]. After 3 seconds, the viewing window should turn completely orange, signaling that ZURNAI has delivered the intended dose of nalmefene.
- Remove ZURNAI from the outer thigh.
- Call 911 immediately after injecting the first dose of ZURNAI.
- Move the person to the recovery position by turning them to their side. Additional supportive and/or resuscitative measures may be helpful while awaiting emergency medical assistance [see Dosage and Administration (2.1)].
- Watch the person carefully. Wait 2 to 5 minutes to see if the person wakes up.
- If the person is not responding or responds and then relapses back into respiratory depression, administer additional doses of ZURNAI every 2 to 5 minutes using a new ZURNAI auto-injector [see Dosage and Administration (2.1)].
- Remain with the person until emergency medical help arrives, even if they wake up.
- Visually inspect the nalmefene solution through the viewing window every 30 days. If the solution is discolored, cloudy, or contains solid particles, replace it with a new ZURNAI.
- Replace ZURNAI before its expiration date.

Healthcare professionals can telephone Purdue Pharma's Medical Information Department (1-888-726-7535) for information on this product.

Manufactured for:
Purdue Pharma L.P.
Stamford, CT 06901-3431

©2024, Purdue Pharma L.P., Stamford, CT 06901-3431

PATIENT INFORMATION
ZURNAI™ (zur nye)
(nalmefene injection)

You and your family members or caregivers should read this Patient Information leaflet before an opioid emergency happens. This information does not take the place of talking with your healthcare provider about your medical condition or your treatment.

What is the most important information I should know about ZURNAI?
ZURNAI is used to temporarily reverse the effects of opioid medicines. The medicine in ZURNAI is not expected to have an effect in people who are not taking opioid medicines. Always carry ZURNAI with you in case of an opioid emergency.

1. Use ZURNAI right away if you or your caregiver think signs or symptoms of an opioid emergency are present, even if you are not sure, because an opioid emergency can cause severe injury or death. Signs and symptoms of an opioid emergency may include:
  - unusual sleepiness and you are not able to awaken the person with a loud voice or by rubbing firmly on the middle of their chest (sternum).
  - breathing problems including slow or shallow breathing in someone difficult to awaken or who looks like they are not breathing.
  - the black circle in the center of the colored part of the eye (pupil) is very small, sometimes called 'pinpoint pupils,' in someone difficult to awaken.
2. Family members, caregivers, or other people who may have to use ZURNAI in an opioid emergency should know where ZURNAI is stored and how to give ZURNAI before an opioid emergency happens. Make sure everyone reads the information contained in the carton as soon as you receive ZURNAI.
3. Call 911 or get emergency medical help right away after giving the first dose of ZURNAI. Rescue breathing or CPR (cardiopulmonary resuscitation) may be given while waiting for emergency medical help.
4. The signs and symptoms of an opioid emergency can return after ZURNAI is given. If this happens, give additional doses of ZURNAI every 2 to 5 minutes using a new ZURNAI auto-injector for each dose and watch the person closely until emergency help arrives.

What is ZURNAI?

- ZURNAI is a prescription medicine used in adults and children 12 years of age and older for the treatment of an opioid emergency such as an overdose or a possible opioid overdose with signs of breathing problems and severe sleepiness or not being able to respond.
- ZURNAI is to be given right away and does not take the place of emergency medical care. Get emergency medical help right away after giving the first dose of ZURNAI, even if the person wakes up.

It is not known if ZURNAI is safe and effective in children younger than 12 years of age for the emergency treatment of known or suspected opioid overdose.

Do not use ZURNAI if you are allergic to nalmefene hydrochloride or any of the ingredients in ZURNAI. See the end of this Patient Information leaflet for a complete list of ingredients in ZURNAI.

Before using ZURNAI, tell your healthcare provider about all of your medical conditions, including if you:

- have heart problems.
- are pregnant or plan to become pregnant. It is not known if ZURNAI will harm your unborn baby.
- are breastfeeding or plan to breastfeed. It is not known if ZURNAI passes into your breast milk.

Tell your healthcare provider about the medicines you take, including prescription and over-the-counter medicines, vitamins, and herbal supplements.

How should I use ZURNAI?
Read the "Instructions for Use" at the end of this Patient Information leaflet for detailed information about the right way to use ZURNAI.

- Use ZURNAI exactly as prescribed by your healthcare provider.
- Each ZURNAI auto-injector contains only 1 dose of medicine and cannot be reused.
- The ZURNAI auto-injector is ready to use. Do not test or prime ZURNAI before use.
- ZURNAI should be injected into the muscle (intramuscular) or underneath the skin (subcutaneous) of the outer thigh. It can be injected through your clothing if needed.

What are the possible side effects of ZURNAI?
ZURNAI may cause serious side effects, including:

- Sudden opioid withdrawal symptoms. In someone who has been using opioids regularly, opioid withdrawal symptoms can happen suddenly after receiving ZURNAI and may include:

- body aches
- diarrhea
- increased heart rate
- fever
- runny nose
- sneezing

- goose bumps
- sweating
- yawning
- nausea or vomiting
- nervousness
- restlessness or irritability

- shivering or trembling
- stomach cramping
- weakness
- increased blood pressure

- Risk of opioid overdose. ZURNAI blocks the effects of opioids and may cause opioid withdrawal in someone who has been using opioids regularly. Do not take large amounts of opioids to try to overcome the opioid-blocking effects of ZURNAI. This could lead to an opioid overdose and death. Call 911 or get emergency medical help right away after using ZURNAI.

The most common side effects of ZURNAI include:

- feeling hot
- nausea
- headache
- dizziness
- chills

- vomiting
- feeling pain from things that are not usually painful (allodynia)
- irregular heartbeat (palpitations)
- ringing in the ear

- ear discomfort
- feeling abnormal
- burning sensation
- hot flush
- irritability

These are not all of the possible side effects of ZURNAI.
Call your doctor for medical advice about side effects. You may report side effects to FDA at 1-800-FDA-1088.

How should I store ZURNAI?

- Store ZURNAI at room temperature between 68°F to 77°F (20°C to 25°C).
- Do not freeze or refrigerate.
- Store ZURNAI in a clean dry place. Protect from light.
- Keep ZURNAI in the carton until use.
- During storage, check ZURNAI through the viewing window of the auto-injector every 30 days. The liquid should be clear, colorless to light yellow. If the ZURNAI liquid is discolored, cloudy, or contains solid particles, replace it with a new ZURNAI.
- Check the expiration date. Replace ZURNAI before the expiration date.

Keep ZURNAI and all medicines out of the reach of children.

General information about the safe and effective use of ZURNAI.
Medicines are sometimes prescribed for purposes other than those listed in a Patient Information leaflet. Do not use ZURNAI for a condition for which it was not prescribed. You can ask your pharmacist or healthcare provider for information about ZURNAI that is written for health professionals.

What are the ingredients in ZURNAI?
Active ingredient: nalmefene
Inactive ingredients: hydrochloric acid to adjust pH, magnesium chloride, and water for injection.
ZURNAI is not made with natural rubber latex.

Manufactured for: Purdue Pharma L.P., Stamford, CT 06901-3431.
For more information, go to www.ZURNAI.com or call 1-888-726-7535.

This Patient Information has been approved by the U.S. Food and Drug Administration.

Issued: 08/2024

INSTRUCTIONS FOR USE

ZURNAI™ (zur nye)
(nalmefene injection)

The Instructions for Use contains information on how to give ZURNAI in response to a known or suspected opioid overdose in adults and children 12 years of age and older. You and your family members or caregivers should read the Instructions for Use that comes with ZURNAI before using it. Talk to your healthcare provider if you and your family members or caregivers have any questions about the use of ZURNAI.

ZURNAI auto-injector parts:

Important information you need to know before injecting ZURNAI

- The ZURNAI auto-injector is ready to use. Do not test or prime ZURNAI before use.
- Each ZURNAI auto-injector contains 1 dose of medicine and cannot be reused.
- Inject ZURNAI into the muscle (intramuscular) or underneath the skin (subcutaneous) of the outer thigh. Do not inject into any other area of the body.

Preparing to inject ZURNAI

- Check person for signs of a suspected overdose:
  - will not wake to voice or touch
  - very sleepy
  - not breathing well
- Check the auto-injector label to make sure you are injecting ZURNAI.
- Check for any visible damage to the auto-injector before using.
- Check the auto-injector to make sure the safety seal is not broken and the blue cap is secure and not missing.
- Check the liquid through the viewing window before using. It should be clear, colorless to light-yellow and free of particles. You may see air bubbles. This is normal.

Injecting ZURNAI

1. Remove the blue cap

- Twist the blue cap counterclockwise to break the safety seal and pull straight off to remove the cap.
- After the blue cap is removed, a few drops of liquid may appear on the needle end. This is normal.
- ZURNAI must be used right away after the safety seal is broken and blue cap is removed. Do not replace the blue cap after it has been removed. If you do not use ZURNAI right away, see Step 5 for instructions on how to throw away ZURNAI.
- Do not touch the needle end of the auto-injector after the blue cap is removed to prevent injury or accidental activation.

2. Position and inject

- Place the needle guard of the auto-injector against the outer thigh. The needle will inject through clothing.
- Push the auto-injector firmly down against the outer thigh until you hear a "click" (the click indicates the start of the injection).
- Hold in place for 3 seconds.

3. Inspect the viewing window

- After holding in place for 3 seconds, the viewing window should turn completely orange. A fully blocked (completely orange) window confirms the injection is complete.
- Remove the auto-injector from the outer thigh.
- Do not replace the blue cap after the injection.
- If the viewing window is not fully blocked after injecting, repeat Steps 1 to 3 using a new ZURNAI auto-injector.

4. Call 911 and watch the person

- Call 911 or get emergency medical help right away after the injection.
- Move the person on their side (recovery position).
  - Hand is supporting their head.
  - Bend their knee.
  - Turn their face to the side.
- Watch the person for response. Wait for 2 to 5 minutes to see if the person wakes up.
- If no response, repeat Steps 1 to 3 using a new ZURNAI auto-injector to give another dose.
- If more ZURNAI auto-injectors are available, Steps 1 to 3 may be repeated every 2 to 5 minutes until the person responds or emergency medical help arrives.
- Stay with the person until medical help arrives, even if the person wakes up.

5. Throw away (dispose of) the used ZURNAI auto-injector

Disposing of (throwing away) ZURNAI

- Put your used ZURNAI auto-injector in a FDA-cleared sharps disposal container right away after use. Do not throw away (dispose of) ZURNAI in your household trash.
- If you do not have an FDA-cleared sharps disposal container, you may use a household container that is:
  - made of a heavy-duty plastic,
  - can be closed with a tight-fitting, puncture-resistant lid, without sharps being able to come out,
  - upright and stable during use,
  - leak resistant, and
  - properly labeled to warn of hazardous waste inside the container.
- When your sharps disposal container is almost full, you will need to follow your community guidelines for the right way to dispose of your sharps disposal container. There may be state or local laws about how you should throw away used needles and syringes. For more information about safe sharps disposal, and for specific information about sharps disposal in the state that you live in, go to the FDA's website at: http://www.fda.gov/safesharpsdisposal.
- Do not dispose of your used sharps disposal container in your household trash unless your community guidelines permit this. Do not recycle your used sharps disposal container.

Important: Always keep the sharps disposal container out of the reach of children.

Storing ZURNAI

- Store ZURNAI at room temperature between 68°F to 77°F (20°C to 25°C).
- Do not freeze or refrigerate.
- Store ZURNAI in a clean dry place. Protect from light.
- Keep ZURNAI in the carton until use.
- During storage, check ZURNAI through the viewing window of the auto-injector every 30 days. The liquid should be clear, colorless to light yellow. If the ZURNAI liquid is discolored, cloudy, or contains solid particles, replace it with a new ZURNAI.
- Check the expiration date. Replace ZURNAI before the expiration date.

Keep ZURNAI and all medicines out of the reach of children.

Manufactured for Purdue Pharma L.P., Stamford CT, 06901-3431. ©2024, Purdue Pharma L.P., Stamford CT 06901-3431 For more information go to www.ZURNAI.com or call 1-888-726-7535. This Instructions for Use has been approved by the U.S. Food and Drug Administration. | Issued: 08/2024

PRINCIPAL DISPLAY PANEL - 1.5 mg/0.5 mL Auto-Injector Label

Zurnai™
(nalmefene injection)
for intramuscular or subcutaneous use
1.5 mg/0.5 mL Auto-Injector

Do not use if solution is discolored or cloudy or contains particles.

Rx Only

Single-dose Auto-Injector.

PRINCIPAL DISPLAY PANEL - 1.5 mg/0.5 mL Auto-Injector Carton

Zurnai™
(nalmefene injection)
for intramuscular or subcutaneous use
1.5 mg/0.5 mL Auto-Injector

Dosage: see Full Prescribing Information
Use for known or suspected opioid overdose in adults and children 12 years of
age and older.

Each single-dose auto-injector device delivers 1.5 mg of nalmefene in 0.5 mL.

Each Zurnai Auto-Injector has only one dose and cannot be re-used.

NDC 59011-962-01
Rx Only

Each carton contains:

- One single-dose Zurnai Auto-Injector
- Full Prescribing Information, including detailed
  Patient Information with Instructions for Use

Manufactured for:
Purdue Pharma L.P. Stamford, CT 06901-3431

306452-0B